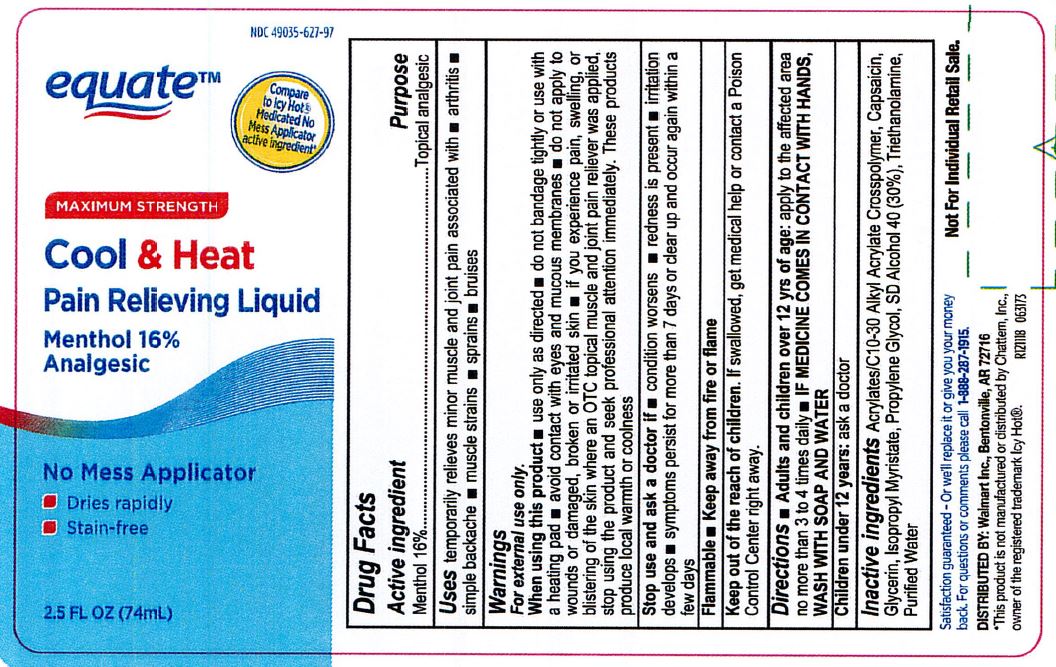 DRUG LABEL: Hot/Cold Menthol 16% Roll-On
NDC: 0395-9131 | Form: LIQUID
Manufacturer: Humco Holding Group, Inc
Category: otc | Type: HUMAN OTC DRUG LABEL
Date: 20231215

ACTIVE INGREDIENTS: MENTHOL 16 mg/100 mL
INACTIVE INGREDIENTS: (C10-C30)ALKYL METHACRYLATE ESTER; PROPYLENE GLYCOL; TROLAMINE; ALCOHOL; CAPSAICIN; ISOPROPYL MYRISTATE; GLYCERIN; WATER

Private Label Hot/Cold Menthol 16% Roll-On

DOSAGE AND ADMINISTRATION

Adults and children over 12 yrs of age: apply to the affected area no more than 3 to 4 times daily

IF MEDICINE COMES IN CONTACT WITH HANDS, WASH WITH SOAP AND WATER.

When using this product: use only as directed. Do not bandage tightly or use with a heating pad. Avoid contact with eyes and mucous membranes. Do not apply to wounds or damaged, broken or irritated skin. If you experience pain, swelling, or blistering of the skin where an OTC topical muscle and joint pain reliever was applied, stop using the product and seek professional attention immediately. These products produce local warmth or coolness.

INACTIVE INGREDIENT

Acrylates/C10-30 Alkyl Acrylate Crosspolymer, Capsaicin, Glycerin, Isopropyl Myristate, Propylene Glycol, SD Alcohol 40 (30%Z), Triethanolamine, Purified Water.

INDICATIONS AND USAGE

Temporarily relieves minor muscle and joint pain associated with arthritis, simple backache, muscle strains, sprains, bruises.

Keep out of reach of children. If swallowed, get medical help or contact a Poison Control Center right away.

PURPOSE

Topical analgesic

ACTIVE INGREDIENT

Menthol 16%